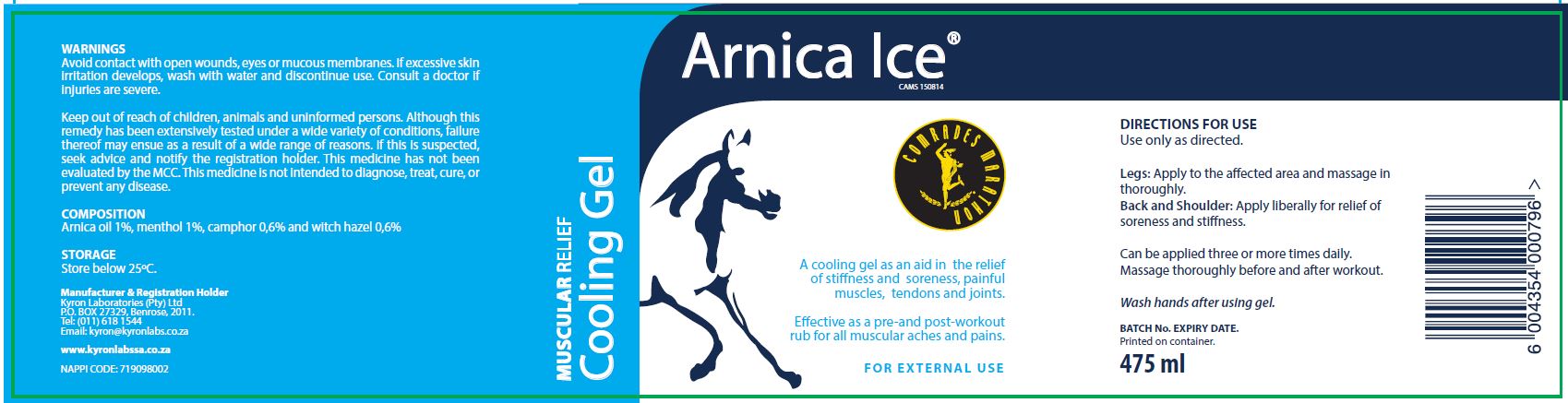 DRUG LABEL: Arnica Ice Cooling
NDC: 70674-001 | Form: GEL
Manufacturer: Kyron Laboratories (pty) Ltd
Category: otc | Type: HUMAN OTC DRUG LABEL
Date: 20160523

ACTIVE INGREDIENTS: CAMPHOR (NATURAL) 6.0 mg/100 mg; MENTHOL 1 mg/100 mg
INACTIVE INGREDIENTS: POLYSORBATE 80; TROLAMINE; PROPYLPARABEN; CARBOMER COPOLYMER TYPE A (ALLYL PENTAERYTHRITOL CROSSLINKED); WATER; WITCH HAZEL; ARNICA MONTANA FLOWER WATER; METHYLPARABEN

WARNINGS

Avoid contact with open wounds, eyes or mucus membrains. If excessive skin irritation develops. Wash with water and discontinue use.
Consult a doctor if injuries are severe.

PURPOSE

Muscular relief cooling gel

ACTIVE INGREDIENT

ARNICA OIL
CAMPHOR
WITCH HAZEL
MENTHOL CRYSTALS

INACTIVE INGREDIENT

CARBOPOL 990
WATER
POLYSORBATE 80
METHYL HYDROXYBENZOATE
PROPYL HYDROXYBENZOATE
TRIETHANOLAMINE 85%

Keep out of reach of children, animals and uniformed persons.
Although this remedy has been extensively tested under a wide variety of conditions, failure thereof may ensue as a result of a wide range of reasons. If this is suspected, seek advice and notify the registration holder.
This medicine has not been evaluated by the MCC.
This medicine is not intended to diagnose, treat, cure or prevent any disease.

DOSAGE AND ADMINISTRATION

Use only as directed

indications and usage